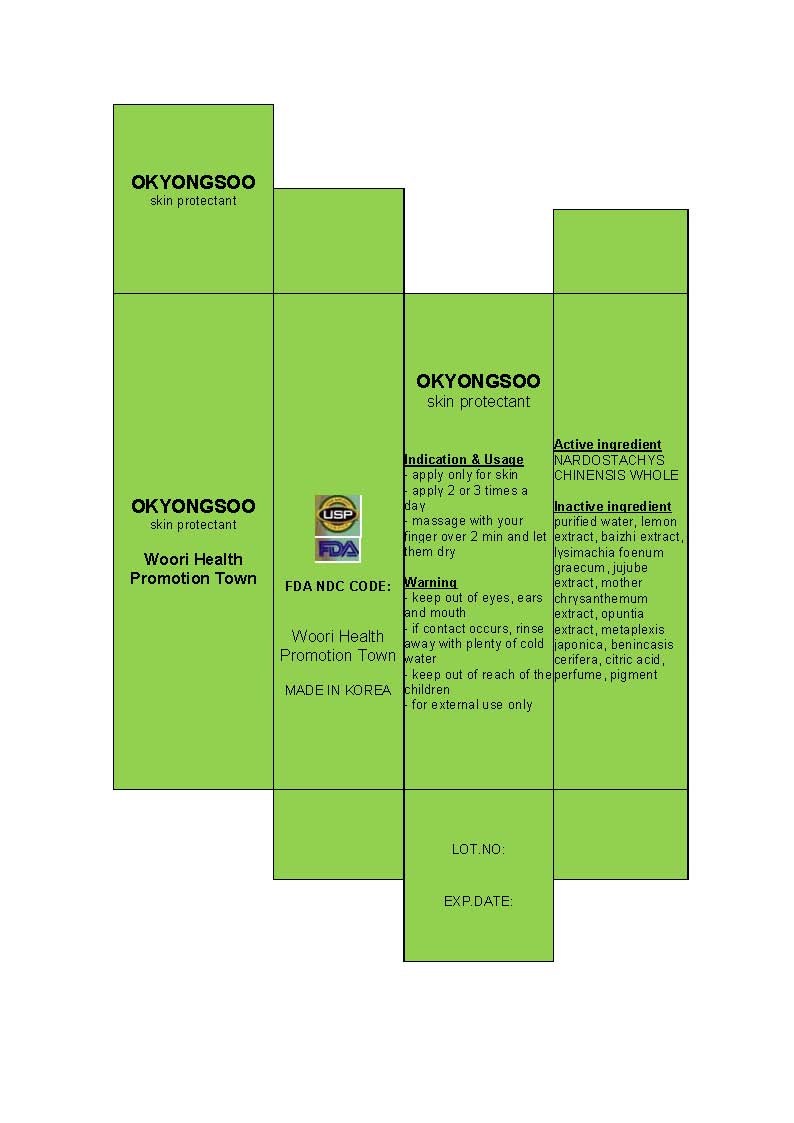 DRUG LABEL: Okyongsoo
NDC: 50973-1001 | Form: LIQUID
Manufacturer: Woori Health Promotion Town
Category: otc | Type: HUMAN OTC DRUG LABEL
Date: 20120618

ACTIVE INGREDIENTS: NARDOSTACHYS CHINENSIS WHOLE 1 mL/100 mL
INACTIVE INGREDIENTS: WATER; JUJUBE FRUIT; CHRYSANTHEMUM X MORIFOLIUM FLOWER; HALIMEDA OPUNTIA; ASCLEPIAS QUADRIFOLIA WHOLE; BENINCASA HISPIDA FRUIT; CITRIC ACID MONOHYDRATE

Drug Facts

active ingredient: NARDOSTACHYS CHINENSIS WHOLE

inactive ingredient: purified water, lemon extract, baizhi extract, lysimachia foenum graecum, jujube extract, mother chrysanthemum extract, opuntia extract, metaplexis japonica, benincasis cerifera, citric acid, perfume, pigment

PURPOSE

skin protectant (anti-wrinkle)

keep out of reach of the children

INDICATIONS AND USAGE

- apply only for skin
- apply 2 or 3 times a day
- massage with your finger over 2 min and let them dry

WARNINGS

- keep out of eyes, ears and mouth
- if contact occurs, rinse away with plenty of cold water

DOSAGE AND ADMINISTRATION

- for external use only